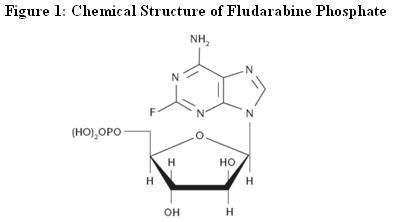 DRUG LABEL: Unknown
Manufacturer: Antisoma Research Limited
Category: prescription | Type: HUMAN PRESCRIPTION DRUG LABELING
Date: 20090218

HIGHLIGHTS OF PRESCRIBING INFORMATION

Fludarabine Phosphate Film-Coated Tablets

WARNING: CNS TOXICITY, HEMOLYTIC ANEMIA, AND PULMONARY TOXICITY

See full prescribing information for complete boxed warning.

- Severe central nervous system toxicity occurred in 36% of patients treated with doses approximately four times greater (96 mg/m^2/day for 5 days to 7 days) than the recommended intravenous dose. This toxicity was seen in ≤0.2% of patients treated at the recommended intravenous dose levels (25 mg/m^2). (5.1)
- Life-threatening and sometimes fatal autoimmune hemolytic anemia has been reported after one or more cycles of treatment. (5.2)
- High incidence of fatal pulmonary toxicity was observed in a clinical investigation of the combination of fludarabine phosphate with pentostatin (deoxycoformycin) for the treatment of refractory chronic lymphocytic leukemia (CLL). (5.3)

1 INDICATIONS AND USAGE

Fludarabine phosphate is a nucleotide metabolic inhibitor indicated as a single agent for the treatment of adult patients with B-cell chronic lymphocytic leukemia (CLL) whose disease has not responded to or has progressed during or after treatment with at least one standard alkylating-agent containing regimen. Studies demonstrating clinical benefit such as prolongation of survival or relief of symptoms have not been performed. A direct comparison of the clinical efficacy and safety of orally administered fludarabine phosphate relative to intravenously administered fludarabine phosphate has not been studied. (1)

2 DOSAGE AND ADMINISTRATION

Note: The oral dose is different than the intravenous dose.

Chronic Lymphocytic Leukemia (CLL) (2.1):

- The recommended adult dose is 40 mg/m^2 administered daily for five consecutive days by the oral route.
- Begin each 5-day course of treatment every 28 days.
  Renal Impairment (2.2):
- Reduce dose by 20% in patients with mild to moderate renal impairment (creatinine clearance 30 to 70 mL/min/1.73 m^2).
- Reduce dose by 50% in patients with severe renal impairment (creatinine clearance < 30 mL/min/1.73 m^2)

3 DOSAGE FORMS AND STRENGTHS

- 10 milligram film-coated tablets. (see 3)

4 CONTRAINDICATIONS

- None

5 WARNINGS AND PRECAUTIONS

- Severe bone marrow suppression, notably anemia, thrombocytopenia and neutropenia. Monitor blood counts before and during treatment. (5.2)
- Infections. Monitor for signs or symptoms of infection. (5.3)
- Tumor lysis syndrome. Take precautions for patients at high risk. (5.4)
- Transfusion-associated graft-versus-host disease. Use only irradiated blood products for transfusions. (5.6)
- Fludarabine phosphate dose should be adjusted in patients with mild to moderate (creatinine clearance 30 to 70 mL/min/1.73 m^2) or severe (creatinine clearance < 30 mL/min/1.73 m^2) renal impairment. (5.7)
- Fetal harm may occur when administered to a pregnant woman. Women of childbearing potential and fertile males must take contraceptive measures during and at least for 6 months after the cessation of therapy. (5.9)

6 ADVERSE REACTIONS

Most common adverse reactions (incidence > 30%) include myelosuppression (neutropenia, thrombocytopenia and anemia). Fever, weakness, infection, pain, cough and anorexia were also reported as common adverse reactions. (6)

7 DRUG INTERACTIONS

- Fludarabine phosphate in combination with pentostatin is not recommended due to the risk of severe pulmonary toxicity. (5.3 and 7.1)

FULL PRESCRIBING INFORMATION

WARNING: CNS TOXICITY, HEMOLYTIC ANEMIA, AND PULMONARY TOXICITY

Severe neurologic effects, including blindness, coma, and death were observed in dose-ranging studies in patients with acute leukemia when fludarabine phosphate was administered at high doses. This severe central nervous system toxicity occurred in 36% of patients treated with doses approximately four times greater (96 mg/m^2/day for 5 days to 7 days) than the recommended intravenous dose (25 mg/m^2/day). Similar severe central nervous system toxicity has been rarely (≤0.2%) reported in patients treated at doses in the range of the dose recommended for chronic lymphocytic leukemia. [See Warnings and Precautions (5.1)] Periodic neurological assessments are recommended.

Instances of life-threatening and sometimes fatal autoimmune hemolytic anemia have been reported after one or more cycles of treatment with fludarabine phosphate. Patients undergoing treatment with fludarabine phosphate should be evaluated and closely monitored for hemolysis. [See Warnings and Precautions (5.2)]

High incidence of fatal pulmonary toxicity was observed in a clinical investigation using fludarabine phosphate in combination with pentostatin (deoxycoformycin) for the treatment of refractory chronic lymphocytic leukemia (CLL). Therefore, the use of fludarabine phosphate in combination with pentostatin is not recommended [See Warnings and Precautions (5.3)]

1 INDICATIONS AND USAGE

Fludarabine phosphate is indicated as a single agent for the treatment of adult patients with B-cell chronic lymphocytic leukemia (CLL) whose disease has not responded to or has progressed during or after treatment with at least one standard alkylating-agent containing regimen. Studies demonstrating clinical benefit such as prolongation of survival or relief of symptoms have not been performed. Studies providing a direct comparison of the clinical efficacy and safety of orally administered fludarabine phosphate relative to intravenously administered fludarabine phosphate have not been performed.

2 DOSAGE AND ADMINISTRATION

2.1 Chronic Lymphocytic Leukemia (CLL)

The oral dose is different than the intravenous dose.

The recommended adult dose of fludarabine phosphate is 40 mg/m^2 administered by mouth daily for five consecutive days. Each 5-day course of treatment should commence every 28 days. Dosage may be decreased or delayed based on evidence of hematologic or nonhematologic toxicity. Physicians should consider delaying or discontinuing the drug if neurotoxicity occurs. Fludarabine phosphate film-coated tablets can be taken either on an empty stomach or with food. The tablets have to be swallowed whole with water; they should not be chewed or broken.

The following table provides guidance for determining the number of tablets of fludarabine phosphate to be administered based on body surface area (BSA):

TABLE 1: SUGGESTED NUMBER OF TABLETS TO BE ADMINISTERED
Body Surface Area (BSA) | Calculated Total Dose Equivalent to 40 mg/m^2 BSA (rounded up or down to nearest 10 mg) | Total Number of Tablets
0.75 – 0.88 | 30 mg | 3
0.89 – 1.13 | 40 mg | 4
1.14 – 1.38 | 50 mg | 5
1.39 – 1.63 | 60 mg | 6
1.64 – 1.88 | 70 mg | 7
1.89 – 2.13 | 80 mg | 8
2.14 – 2.38 | 90 mg | 9
2.39 – 2.50 | 100 mg | 10

A number of clinical settings may predispose to increased toxicity from fludarabine phosphate. These include advanced age, renal insufficiency, and bone marrow impairment. Such patients should be monitored closely for excessive toxicity and the dose modified accordingly. The optimal duration of treatment has not been clearly established. It is recommended that three additional cycles of fludarabine phosphate be administered following the achievement of a maximal response and then the drug should be discontinued.

2.2 Renal Impairment

- Reduce dose by 20% in patients with mild to moderate renal impairment (creatinine clearance 30 to 70 mL/min/1.73 m^2). [See Warnings and Precautions (5.7)]
- Reduce dose by 50% in patients with severe renal impairment (creatinine clearance < 30 mL/min/1.73 m^2). [See Warnings and Precautions (5.7)]

3 DOSAGE FORMS AND STRENGTHS

10 mg film-coated tablets that are capsule shaped and salmon pink in color, marked on one side with ‘LN’ in a regular hexagon.

4 CONTRAINDICATIONS

None

5 WARNINGS AND PRECAUTIONS

5.1 Neurotoxicity

Dose-dependent neurotoxicity has been observed with fludarabine phosphate. Dose levels approximately 4 times greater (96 mg/m^2/day for 5 days to 7 days) than the recommended intravenous dose (25 mg/m^2/day for 5 days) were associated with a syndrome characterized by delayed blindness, coma and death. Symptoms appeared from 21 days to 60 days following the last dose. Thirteen of 36 patients (36.1%) who received fludarabine phosphate intravenously at high doses (≥ 96 mg/m^2/day for 5 days to 7 days per course) developed severe neurotoxicity, while only one of 443 patients (0.2%) who received the drug intravenously at low doses (≤ 40 mg/m^2/day for 5 days per course) developed toxicity. In the pivotal clinical study conducted with fludarabine phosphate film-coated tablets administered at 40 mg/m^2, severe impairment of consciousness was reported in one patient. The effect of chronic administration of fludarabine phosphate on the central nervous system is unknown; however, patients have received the recommended dose for up to 15 courses of therapy. Physicians should consider delaying or discontinuing the drug if neurotoxicity occurs.

5.2 Bone Marrow Suppression

Severe bone marrow suppression, notably anemia, thrombocytopenia and neutropenia, has been reported in patients treated with fludarabine phosphate. In a study in adult solid tumor patients, the median time to nadir counts was 13 days (range, 3 days to 25 days) for granulocytes and 16 days (range, 2 days to 32 days) for platelets. Most patients had hematologic impairment at baseline either as a result of disease or as a result of prior myelosuppressive therapy. Cumulative myelosuppression may be seen. While chemotherapy-induced myelosuppression is often reversible, administration of fludarabine phosphate requires careful hematologic monitoring.

Several instances of trilineage bone marrow hypoplasia or aplasia resulting in pancytopenia, sometimes resulting in death, have been reported in adult patients. The duration of clinically significant cytopenia in the reported cases has ranged from approximately 2 months to approximately 1 year. These episodes have occurred both in previously treated or untreated patients. One case of pancytopenia was reported in the pivotal clinical study conducted with oral fludarabine phosphate tablets.

Instances of life-threatening and sometimes fatal autoimmune hemolytic anemia have been reported to occur after one or more cycles of treatment with fludarabine phosphate in patients with or without a previous history of autoimmune hemolytic anemia or a positive Coombs’ test and who may or may not be in remission from their disease. Steroids may or may not be effective in controlling these hemolytic episodes. The majority of patients rechallenged with fludarabine phosphate developed a recurrence in the hemolytic process. The mechanism(s) which predispose patients to the development of this complication has not been identified. Patients undergoing treatment with fludarabine phosphate should be evaluated and closely monitored for hemolysis.

5.3 Pulmonary Toxicity

A high incidence of fatal pulmonary toxicity was observed in a clinical investigation using fludarabine phosphate in combination with pentostatin (deoxycoformycin) for the treatment of refractory chronic lymphocytic leukemia (CLL) in adults. Therefore, the use of fludarabine phosphate in combination with pentostatin is not recommended.

5.4 Infections

Of 133 adult patients with CLL who received intravenous fludarabine phosphate in two clinical trials, there were 29 fatalities during study. Approximately 50% of the fatalities were due to infection and 25% due to progressive disease. Of 183 adult patients with CLL that received oral fludarabine phosphate in two clinical trials, there were 13 deaths. Approximately 50% of the deaths were due to progressive disease, while two patient deaths (15%) were attributed to infection. Monitor for signs and symptoms of infection.

5.5 Tumor Lysis Syndrome

Tumor lysis syndrome associated with fludarabine phosphate treatment has been reported in patients with CLL with large tumor burdens. Since fludarabine phosphate can induce a response as early as the first week of treatment, precautions should be taken in those patients at risk of developing this complication.

5.6 Use of Transfusions

Transfusion-associated graft-versus-host disease has been observed rarely after transfusion of non-irradiated blood in fludarabine phosphate treated patients. Consideration should, therefore, be given to the use of irradiated blood products in those patients requiring transfusions while undergoing treatment with fludarabine phosphate.

5.7 Renal Impairment

Fludarabine phosphate must be administered cautiously in patients with renal impairment. Following dosing of the intravenous product, the total body clearance of 2-fluoro-ara-A has been shown to be directly correlated with creatinine clearance. Patients with mild to moderate impairment of renal function (creatinine clearance 30 to 70 mL/min/1.73 m^2) should have their oral fludarabine phosphate dose reduced by 20% and be monitored closely. Patients with severe impairment of renal function (creatinine clearance < 30 mL/min/1.73 m^2) should have their oral fludarabine phosphate dose reduced by 50% and be monitored closely.

5.8 Monitoring

- Hematologic and Nonhematologic Toxicity

Fludarabine phosphate is an antineoplastic agent with potentially significant toxic side effects. Patients undergoing therapy should be closely observed for signs of hematologic and nonhematologic toxicity. Periodic assessment of peripheral blood counts is recommended to detect the development of anemia, neutropenia and thrombocytopenia.

- Hematopoietic Suppression

During treatment, the patient’s hematologic profile (particularly neutrophils and platelets) should be monitored regularly to determine the degree of hematopoietic suppression.

- Infections

Patients treated with fludarabine phosphate appear to be at an increased risk of infection. Monitor for signs and symptoms of infection.

5.9 Pregnancy

Based on its mechanism of action, fludarabine phosphate can cause fetal harm when administered to a pregnant woman. Fludarabine phosphate administered to rats and rabbits during organogenesis caused an increase in resorptions, skeletal and visceral malformation, and decreased fetal body weights. If fludarabine phosphate is used during pregnancy, or if the patient becomes pregnant while taking this drug, the patient should be apprised of the potential hazard to the fetus. Women of childbearing potential should be advised to avoid becoming pregnant. Women of childbearing potential and fertile males must take contraceptive measures during and at least for 6 months after the cessation of therapy.
[see Use in Specific Populations (8.1)].

6 ADVERSE REACTIONS

6.1 Clinical Trials Experience

Because clinical trials are conducted under widely varying conditions, adverse reaction rates observed in the clinical trials of a drug cannot be directly compared to rates in the clinical trials of another drug and may not reflect the rates observed in practice.

The data described below reflect exposure to fludarabine phosphate tablets in 159 patients exposed to the drug. Fludarabine phosphate tablets were studied primarily in Study 1 in 78 patients with CLL who received prior therapy and in Study 2 in 81 patients with CLL who had not received prior therapy.

Based on experience with the intravenous and oral use of fludarabine phosphate, the most common adverse reactions include myelosuppression (neutropenia, thrombocytopenia and anemia), fever and chills, infection, and nausea and vomiting. Other commonly reported events include malaise, fatigue, anorexia, and weakness. Serious opportunistic infections have occurred in patients with CLL treated with fludarabine phosphate. The most frequently reported adverse reactions and those reactions which are more clearly related to the drug, as reported in clinical studies conducted with intravenous and oral fludarabine phosphate, are arranged below according to body system.

Hematopoietic Systems

Hematologic events (neutropenia, thrombocytopenia, and/or anemia) were reported in the majority of patients with CLL treated with fludarabine phosphate. During intravenous fludarabine phosphate treatment of 133 patients with CLL, the absolute neutrophil count decreased to less than 500/mm^3 in 59% of patients, hemoglobin decreased from pretreatment values by at least 2 grams percent in 60%, and platelet count decreased from pretreatment values by at least 50% in 55%. Among 78 patients with B-CLL who were treated with oral fludarabine phosphate, the absolute neutrophil count decreased to less than 500/mm^3 in 37% of patients, hemoglobin decreased from pretreatment values by at least 2 grams percent in 14%, and platelet count decreased from pretreatment values by at least 50% in 17% of patients. Myelosuppression may be severe, cumulative, and may affect multiple cell lines. Bone marrow fibrosis occurred in one CLL patient treated with fludarabine phosphate intravenously. In the pivotal oral fludarabine phosphate study (Study 1), there was one report of a non-fatal case of pancytopenia. Similarly, there was one case of non-fatal pancytopenia reported among the 133 patients with CLL treated with intravenous fludarabine phosphate.

Life-threatening and sometimes fatal autoimmune hemolytic anemias have been reported to occur in patients receiving fludarabine phosphate. [See Warnings and Precautions (5.2)] The majority of patients rechallenged with fludarabine phosphate developed a recurrence in the hemolytic process.

Metabolic

Tumor lysis syndrome has been reported in patients with CLL treated with fludarabine phosphate for injection. This complication may include hyperuricemia, hyperphosphatemia, hypocalcemia, metabolic acidosis, hyperkalemia, hematuria, urate crystalluria, and renal failure. The onset of this syndrome may be heralded by flank pain and hematuria.

Nervous System

Objective weakness, agitation, confusion, visual disturbances, and coma have occurred in patients with CLL treated with fludarabine phosphate at the recommended dose. Peripheral neuropathy and one case of wrist-drop have been observed with intravenous administration of fludarabine phosphate. In Study 1 for oral fludarabine phosphate, there was one report of severe impairment of consciousness that presented concurrent with hemolytic anemia. This patient had enrolled in the study with pre-existing peripheral neurotoxicity. [See Warnings and Precautions (5.1)]

Pulmonary System

Pneumonia, a frequent manifestation of infection in patients with CLL, was observed in two clinical trials conducted with intravenous fludarabine phosphate (16% and 22%) and in two clinical trials with oral fludarabine phosphate (8% and 3%). Pulmonary hypersensitivity reactions to fludarabine phosphate characterized by dyspnea, cough and interstitial pulmonary infiltrate have been observed. In Study 1 conducted with oral fludarabine phosphate, severe pulmonary toxicity was reported in 5 of 78 patients, often in conjunction with respiratory or pulmonary infections and hence not regarded as isolated drug related pulmonary toxicity.

Gastrointestinal System

Gastrointestinal disturbances such as nausea and vomiting, anorexia, diarrhea, stomatitis and gastrointestinal bleeding have been reported in patients treated with fludarabine phosphate. Nausea and vomiting occurred in up to 38% of patients following treatment with oral fludarabine phosphate in the clinical trials.

Cardiovascular

Edema has been frequently reported. One patient developed a pericardial effusion possibly related to treatment with fludarabine phosphate. No other severe cardiovascular events were considered to be drug related.

Genitourinary System

Hemorrhagic cystitis has been reported in patients treated intravenously with fludarabine phosphate.

Skin

Skin toxicity, consisting primarily of skin rashes, has been reported in patients treated with oral and intravenous fludarabine phosphate.

Data in Table 2 are derived from the 159 patients with CLL who received fludarabine phosphate in Study 1 and Study 2.

TABLE 2: Incidence (≥5%) of Non-Hematologic Adverse Reactions in Patients with CLL Treated with Fludarabine Phosphate Tablets
ADVERSE REACTIONS | Study 1 (N=78) % | Study 2 (N=81) %
ANY ADVERSE REACTION | 82 | 89
BODY AS A WHOLE | 59 | 77
FEVER | 26 | 11
INFECTION | 12 | 17
PAIN | 5 | 19
FLU SYNDROME | 8 | 5
DIAPHORESIS | 8 | 0
NEUROLOGICAL | 19 | 41
WEAKNESS/FATIGUE (ASTHENIA) | 13 | 31
SWEATING INCREASED | 0 | 14
HEADACHE | 9 | 9
PULMONARY | 37 | 53
COUGH | 21 | 0
COUGH INCREASED | 0 | 6
PNEUMONIA | 8 | 3
DYSPNEA | 1 | 5
SINUSITIS | 1 | 5
UPPER RESPIRATORY INFECTION | 9 | 14
RHINITIS | 3 | 11
BRONCHITIS | 6 | 9
METABOLIC AND NUTRITIONAL | 3 | 31
WEIGHT DECREASED | 1 | 6
LACTIC DEHYDROGENASE INCREASED | 0 | 6
PERIPHERAL EDEMA | 0 | 7
GASTROINTESTINAL | 41 | 28
NAUSEA | 5 | 1
DIARRHEA | 6 | 5
ANOREXIA | 19 | 0
ABDOMINAL PAIN | 8 | 10
CUTANEOUS | 22 | 25
RASH | 5 | 4
SKIN DISORDER | 0 | 6
HERPES SIMPLEX | 8 | 7
GENITOURINARY | 8 | 14
URINARY TRACT INFECTION | 4 | 5
CARDIOVASCULAR | 14 | 17
CHEST PAIN | 0 | 5
MUSCULOSKELETAL | 10 | 19
BACK PAIN | 4 | 9

6.2 Post Marketing Experience

The following adverse reactions have been identified during post approval use of oral fludarabine phosphate. Because these reactions are reported voluntarily from a population of uncertain size, it is not always possibly to reliably estimate their frequency or establish a causal relationship to drug exposure.

Hematopoietic Systems

Several instances of trilineage bone marrow hypoplasia or aplasia resulting in pancytopenia, sometimes resulting in death, have been reported in post-marketing surveillance. The duration of clinically significant cytopenia in the reported cases has ranged from approximately 2 months to approximately 1 year. These episodes have occurred both in previously treated or untreated patients.

Nervous System

In post-marketing experience, cases of progressive multifocal leukoencephalopathy have been reported. Most cases had a fatal outcome. Many of these cases were confounded by prior and/or concurrent chemotherapy. The median time to onset was approximately one year.

Pulmonary System

In post-marketing experience, cases of severe pulmonary toxicity have been observed with fludarabine phosphate use which resulted in acute respiratory distress syndrome, respiratory distress, pulmonary hemorrhage, pulmonary fibrosis, and respiratory failure. After exclusion of an infectious origin, some patients experienced symptom improvement with corticosteroids.

7 DRUG INTERACTIONS

7.1 Pentostatin

The use of fludarabine phosphate in combination with pentostatin is not recommended due to the risk of severe pulmonary toxicity. [See Warnings and Precautions (5.6)]

8 USE IN SPECIFIC POPULATIONS

8.1 Pregnancy

“Pregnancy Category D. See ‘Warnings and Precautions’ section.”

Based on its mechanism of action, fludarabine phosphate can cause fetal harm when administered to a pregnant woman. There are no adequate and well-controlled studies of fludarabine phosphate in pregnant women. Fludarabine phosphate was embryolethal and teratogenic in both rats and rabbits. If fludarabine phosphate is used during pregnancy, or if the patient becomes pregnant while taking this drug, the patient should be apprised of the potential hazard to the fetus. Women of childbearing potential should be advised to avoid becoming pregnant. Women of childbearing potential and fertile males must take contraceptive measures during and at least for 6 months after the cessation of therapy.

In rats, repeated intravenous doses of fludarabine phosphate at 1.5 times and 4.5 times the recommended human oral dose (40 mg/m^2) administered during organogenesis caused an increase in resorptions, skeletal and visceral malformations (cleft palate, exencephaly, and fetal vertebrae deformities) and decreased fetal body weights. Maternal toxicity was not apparent at 1.5 times the human oral dose, and was limited to slight body weight decreases at 4.5 times the human oral dose. In rabbits, repeated intravenous doses of fludarabine phosphate at 2.4 times the human oral dose administered during organogenesis increased embryo and fetal lethality as indicated by increased resorptions and a decrease in live fetuses. A significant increase in malformations including cleft palate, hydrocephaly, adactyly, brachydactyly, fusions of the digits, diaphragmatic hernia, heart/great vessel defects, and vertebrae/rib anomalies were seen in all dose levels (≥ 0.3 times the human oral dose).

8.3 Nursing Mothers

It is not known whether fludarabine phosphate is excreted in human milk. Because many drugs are excreted in human milk and because of the potential for serious adverse reactions including tumorgenicity in nursing infants, a decision should be made to discontinue nursing or discontinue the drug, taking into account the importance of the drug to the mother.

8.4 Pediatric Use

Safety and effectiveness in pediatric patients have not been established.

8.5 Geriatric Use

Of 78 previously treated patients with B-CLL treated with oral fludarabine phosphate 50% were ≥ age 65 and 3% were ≥ age 75. The response rate was generally lower among patients age 65 and older. Among previously treated patients (Study 1) age 65 and older, the overall objective response, according to standardized response criteria developed by the National Cancer Institute CLL Working Group (NCI criteria), was 41%. The safety profile among younger and older patients on study was similar. Other reported clinical experience has not identified differences in responses or safety between older and younger patients.

8.6 Patients with Renal Impairment

In patients receiving intravenous fludarabine phosphate, the total body clearance of the metabolite 2-fluoro-ara-adenine (2F-ara-A) correlated with the creatinine clearance, indicating the importance of the renal excretion pathway for the elimination of the drug. Renal clearance represented approximately 40% of the total body clearance. Patients with mild to moderate renal impairment (30 to 70 mL/min/1.73 m^2) receiving 20% reduced fludarabine phosphate dose had a similar exposure compared to patients with normal renal function receiving the recommended dose (AUC; 21 nM•h/mL versus 20 nM•h/mL). Two patients with severe renal impairment (< 30 mL/min/1.73 m^2) receiving 40% reduced fludarabine phosphate dose had a 40% increase in exposure compared to patients with normal renal function receiving the recommended dose. The mean total body clearance was 172 mL/min for patients with normal renal function, 124 mL/min for patients with mild to moderately impaired renal function, and 71 mL/min for the two patients with severe renal impairment.

10 OVERDOSAGE

High doses of fludarabine phosphate [See Indications and Usage (1.1) and Warnings and Precautions (5.1)] have been associated with an irreversible central nervous system toxicity characterized by delayed blindness, coma and death. High doses are also associated with severe thrombocytopenia and neutropenia due to bone marrow suppression. There is no known specific antidote for fludarabine phosphate overdosage. Treatment consists of drug discontinuation and supportive therapy. In Study 2, two patients ingested an overdose of 20% to 33% of oral fludarabine phosphate. No serious side effects were reported.

11 DESCRIPTION

The chemical name for fludarabine phosphate is 9H-Purin-6-amine, 2-fluoro-9-(5-O-phosphono-ß-D-arabinofuranosyl)(2-fluoro-ara-AMP). The molecular formula of fludarabine phosphate is C10H13FN5O7P (MW 365.2) and the structure is provided in Figure 1

Fludarabine phosphate film-coated tablets for oral administration contain fludarabine phosphate, a fluorinated nucleotide analog of the antiviral agent vidarabine, 9-beta -D-arabinofuranosyladenine (ara-A) that is relatively resistant to deamination by adenosine deaminase. Each tablet contains 10 mg of the active ingredient fludarabine phosphate. The tablet core consists of microcrystalline cellulose, lactose monohydrate, colloidal anhydrous silicon dioxide, croscarmellose sodium and magnesium stearate. The film-coat contains hypromellose, talc, titanium dioxide (E171) and ferric oxide pigment (red/E172, yellow/E172).

12 CLINICAL PHARMACOLOGY

12.1 Mechanism of Action

Fludarabine phosphate (2F-ara-AMP) is a synthetic purine nucleotide antimetabolite agent. Upon administration, 2F-ara-AMP is rapidly dephosphorylated in the plasma to 2F-ara-A, which then enters into the cell. Intracellularly, 2F-ara-A is converted to the 5'-triphosphate, 2-fluoro-ara-ATP (2F-ara-ATP). 2F-ara-ATP competes with deoxyadenosine triphosphate for incorporation into DNA. Once incorporated into DNA, 2F-ara-ATP functions as a DNA chain terminator, inhibits DNA polymerase alpha, gamma, and delta, and inhibits ribonucleoside diphosphate reductase. 2F-ara-A also inhibits DNA primase and DNA ligase I. The mechanism of action of this antimetabolite is not completely characterized and may be multi-faceted.

12.2 Pharmacodynamics

Cardiac Electrophysiology

In a randomized, uncontrolled, open-label, parallel study, patients with B-cell CLL were administered a single dose of oral fludarabine phosphate 40 mg/m^2 (n = 42) or intravenous fludarabine phosphate 25 mg/m^2 (n=14). The maximum increase in the baseline-corrected mean change in QTcI (individual-corrected QT interval) following treatment with oral fludarabine phosphate was less than 10 milliseconds.

12.3 Pharmacokinetics

Studies with the intravenous product have demonstrated that fludarabine phosphate is converted to the active metabolite, 2F-ara-A. Clinical pharmacology studies have focused on 2F-ara-A pharmacokinetics.

Following administration of the intravenous product, systemic plasma clearance of 2F-ara-A is approximately 117 mL/min to 145 mL/min. After five daily 30 minute intravenous infusions of 25 mg 2F-ara- AMP/m^2 to cancer patients, trough concentrations of 2F-ara-A increased by a factor of about 2. The terminal half-life of 2F-ara-A was approximately 20 hours. Plasma protein binding of 2F-ara-A was approximately 19% to 29%. A correlation was noted between the degree of absolute granulocyte count nadir and increased area under the concentration x time curve (AUC).

2F-ara-A exhibits dose proportional increases in AUC and Cmax after single oral doses of 50 mg, 70 mg or 90 mg of 2F-ara-AMP. Cmax of 2F-ara-A occurs 1 hour to 2 hours after single or multiple oral doses and is approximately 20 % to 30 % of the maximum plasma concentrations produced at the end of a 30 minute intravenous infusion of the same dose. The absolute oral bioavailability of 2F-ara-A is 50 - 65% following single and repeated doses of the immediate release tablet formulation. Similar systemic exposure (AUC) was observed after a single 40 mg/m^2 fludarabine phosphate oral dose and a single 25 mg/m^2 fludarabine phosphate intravenous dose. The terminal half-life of 2F-ara-A was similar to that following intravenous administration; approximately 20 hours. The Cmax, AUC and terminal half-life of 2F-ara-A are unaffected when administered with a high fat meal, although Tmax is slightly delayed from 1.3 hours to 2.2 hours.

Following intravenous administration, renal clearance of 2F-ara-A represents approximately 40% of the total body clearance of fludarabine phosphate, and total body clearance is inversely correlated with serum creatinine and creatinine clearance. In two patients with median creatinine clearance of 22 mL/min/1.73 m^2, 2F-ara-A clearance was reduced by 56%. Dosage adjustment based on creatinine clearance is recommended as follows:

Reduce dose by 20% in patients with mild to moderate renal impairment (creatinine clearance 30 to 70 mL/min/1.73 m^2). [See Warnings and Precautions (5.7)]

Reduce dose by 50% in patients with severe renal impairment (creatinine clearance < 30 mL/min/1.73 m^2). [See Warnings and Precautions (5.7)]

13 NONCLINICAL TOXICOLOGY

13.1 Carcinogenesis, Mutagenesis, Impairment of Fertility

No animal carcinogenicity studies with fludarabine phosphate have been conducted.

Fludarabine phosphate is a clastogen.

Fludarabine phosphate was clastogenic in vitro to Chinese hamster ovary cells (chromosome aberration assay) in the presence of metabolic activation and induced sister chromatid exchanges both in the presence and absence of metabolic activation. In addition, fludarabine phosphate was clastogenic in vivo (mouse micronucleus assay) but was not mutagenic to germ cells (dominant lethal test in male mice). Fludarabine phosphate was not mutagenic to bacteria (Ames test) or mammalian cells either in the presence or absence of metabolic activation.

Studies in mice, rats and dogs have demonstrated dose-related adverse effects on the male reproductive system. Observations consisted of a decrease in mean testicular weights in mice and rats with a trend toward decreased testicular weights in dogs and degeneration and necrosis of spermatogenic epithelium of the testes in mice, rats and dogs.

14 CLINICAL STUDIES

Study 1, a single-arm, open-label study of fludarabine phosphate film-coated tablets was conducted in 78 adult patients with CLL refractory to at least one prior standard alkylating-agent containing regimen. In this multicenter study patients were treated with oral fludarabine phosphate at a dose of 40 mg/m^2 daily for 5 days every 28 days. The patient population median age was 64.5 years and consisted of 72% males and 28% females. Ninety-nine percent of the patients were Caucasian. The Rai stage for patients entering the study was: Stage 0 (3.9%), Stage I (20.5%), Stage II (32.1%), Stage III (11.5%), and Stage IV (32.1%). The mean number of treatment cycles was 5.1 with a mean daily dose of fludarabine phosphate of 38 mg/m^2. The overall objective response, according to standardized response criteria developed by the National Cancer Institute CLL Working Group (NCI criteria), was 51 %, including 18% complete responses and 33% partial responses. The overall response rate, according to standardized criteria developed by the International Workshop on CLL (IWCLL criteria), was 46%, including 21% complete responses and 26% partial responses. Data on duration of response was not collected.

In Study 2, a supportive single-arm, open-label study, fludarabine phosphate tablets were administered to 81 previously untreated patients with B-CLL. In this multicenter study each patient was treated with oral fludarabine phosphate at a dose of 40 mg/m^2 daily for 5 days every 28 days. The patient population median age was 64.0 years and consisted of 63% males and 37% females. Ninety-nine percent of the patients were Caucasian. The Rai stage for patients entering the study was: Stage 0 (3.7%), Stage I (37.0%), Stage II (37.0%), Stage III (9.9%), and Stage IV (12.3%). The mean number of treatment cycles was 5.9 with a mean daily dose per patient of 71 mg to 74 mg. The overall responses rate, according to NCI criteria, was 80%, including 12% complete responses and 68% partial responses. The overall response rate, according to IWCLL criteria, was 72%, including 37% complete responses and 35% partial responses. The median duration of response was 22.9 months.

Study 3 was a supportive randomized controlled open label study in patients with previously untreated B-CLL that included fludarabine phosphate monotherapy and fludarabine phosphate combination therapy arms. In this study 107 evaluable patients received fludarabine phosphate 40mg/m^2 orally daily for 5 days every 28 days. The overall response rate according to modified NCI criteria was 74% and the CR plus nodular PR rate was 41%.

15 REFERENCES

1. Preventing Occupational Exposures to Antineoplastic and Other Hazardous Drugs in Health Care Settings. NIOSH Alert 2004-165.
2. OSHA Technical Manual, TED 1-0.15A, Section VI: Chapter 2. Controlling Occupational Exposure to Hazardous Drugs. OSHA, 1999.
  http://www.osha.gov/dts/osta/otm/otm_vi/otm_vi_2.html
3. American Society of Health-System Pharmacists. ASHP guidelines on handling hazardous drugs. Am J Health-Syst Pharm. 2006;63:1172-1193.
4. Polovich, M., White, J. M., & Kelleher, L.O. (eds.) 2005. Chemotherapy and biotherapy guidelines and recommendations for practice (2nd. ed.) Pittsburgh, PA: Oncology Nursing Society.

16 HOW SUPPLIED/STORAGE AND HANDLING

HOW SUPPLIED

Fludarabine phosphate is supplied in 10 milligram tablets that are film-coated, capsule shaped, salmon pink in color, and marked on one side with ‘LN’ in a regular hexagon. Each film-coated tablet contains 10 mg fludarabine phosphate. The tablets are supplied in blisters, each blister strip containing 5 tablets. Packages of 15 and 20 tablets are available in child-resistant containers.

NDC 45414-311-15: 15 - 10 milligram film-coated tablets per container. Each film-coated tablet is packaged in an individual blister package; 5 tablets per blister strip; 3 blister strips packaged in a plastic bottle with a child-resistant container closure; each bottle is packaged in an individual chip-board carton.

NDC 45414-311-20: 20 - 10 milligram film-coated tablets per container. Each film-coated tablet is packaged in an individual blister package; 5 tablets per blister strip; 4 blister strips packaged in a plastic bottle with a child-resistant container closure; each bottle is packaged in an individual chip-board carton.

STORAGE

Store under normal lighting conditions at 25°C (77°F); excursions permitted to 15-30°C (59-86°F) [see USP controlled room temperature].

HANDLING AND DISPOSAL

Procedures for proper handling and disposal should be considered. Consideration should be given to handling and disposal according to guidelines issued for cytotoxic drugs. Several guidelines on this subject have been published.^1-4 Caution should be exercised in the handling of fludarabine phosphate. Do not crush tablets. Avoid exposure by direct contact of the skin or mucous membranes or by inhalation. If contact occurs, wash thoroughly with soap and water or wash the eyes immediately with gently flowing water for at least 15 minutes. Consult healthcare provider in case of a skin reaction or if the drug gets in the eyes.

17 PATIENT COUNSELING INFORMATION

17.1 Bone Marrow Suppression

Inform patients that fludarabine phosphate decreases blood cell counts such as white blood cells, platelets, and red blood cells. Thus, it is important that periodic assessment of their blood count be performed to detect the development of neutropenia, thrombocytopenia and anemia. [See Warnings and Precautions (5.2)]

17.2 Infections

Instruct patients to notify their physician promptly if fever or other signs of infection such as chills, cough, or burning pain on urination occurs while on therapy. [See Warnings and Precautions (5.4)]

17.3 Pregnancy

Women of childbearing potential and fertile males must take contraceptive measures during and at least for 6 months after the cessation of therapy.

Fludarabine phosphate may cause fetal harm when administered to a pregnant woman. [See Warnings and Precautions (5.9)]

17.4 Handling and Disposal

Instruct patients that caution should be exercised in the handling of fludarabine phosphate. Do not crush tablets. Avoid exposure by direct contact of the skin or mucous membranes or by inhalation. If contact occurs, wash thoroughly with soap and water or wash the eyes immediately with gently flowing water for at least 15 minutes. Consult healthcare provider in case of a skin reaction or if the drug gets in the eyes. Ask your healthcare provider or pharmacist for directions about how to safely dispose of fludarabine phosphate.

Manufactured for: Antisoma Research Limited, Cambridge, MA 02139

Manufactured by: Bayer Schering Pharma AG, Berlin, Germany

Patient Package Insert

[TRADENAME] (phonetic spelling)
(oral fludarabine phosphate film-coated tablets)

Read this Patient Information leaflet before you start taking [TRADENAME] and each time you get a refill. There may be new information. This information does not take the place of talking with your healthcare provider about your medical condition or your treatment.

What Is [TRADENAME]?

[TRADENAME] is a prescription anticancer medicine that slows or stops the growth of cancer cells in adults with chronic lymphocytic leukemia (CLL). [TRADENAME] also stops or slows the growth of some healthy cells. This can cause side effects that you should know about and report to your healthcare provider.

[TRADENAME] has not been studied in children.

What is the most important information I should know about [TRADENAME]?

On rare occasions people taking [TRADENAME] can have life-threatening symptoms. If you:

- have problems seeing
- feel very sleepy, tired, or confused
- have shortness of breath or have trouble breathing
- have yellow skin or dark urine

Tell your healthcare provider right away.

What should I tell my healthcare provider before taking [TRADENAME]?

Before taking [TRADENAME], tell your healthcare provider about all of your medical conditions, including if you:

- have kidney problems
- have bleeding problems
- are pregnant or plan to become pregnant. It is not known if [TRADENAME] will harm your unborn baby. Talk to your doctor if you are pregnant or plan to become pregnant. Women should not get pregnant during treatment with [TRADENAME] because the unborn baby may be harmed. Both men and women must take contraceptive measures during and for at least six months after cessation of therapy. Call your doctor right away if you become pregnant during or in the six months after treatment with [TRADENAME].
- are breast- feeding or plan to breast-feed. It is not known if [TRADENAME] passes into your breast milk. You and your healthcare provider should decide if you will take [TRADENAME] or breast-feed. You should not do both.

Tell your healthcare provider about all the medicines you take including prescription and non-prescription medicines, vitamins, and herbal supplements. Using [TRADENAME] with certain other medicines may affect each other. Using [TRADENAME] with other medicines may cause serious side effects.

Know the medicines you take. Keep a list of them with you to show your healthcare provider.

How should I take [TRADENAME]?

- Take [TRADENAME] exactly as your healthcare provider tells you to take it.
- Your healthcare provider will tell you how much and when to take [TRADENAME].
- [TRADENAME] can be taken with or without food.
- [TRADENAME] have to be swallowed whole with water; they should never be chewed, crushed, or broken. If you cannot swallow [TRADENAME] whole, ask your healthcare provider if you can take another form of fludarabine.
- If you miss a dose call your healthcare provider.
- If you take too much call your healthcare provider.

What should I avoid while taking [TRADENAME]?

- Do not allow other people or pets to touch or take [TRADENAME].
- Avoid letting the tablets (whole or broken) touch your skin
- Do not chew tablets or hold them in your mouth. Swallow tablets right away.
- Do not breathe in any powder or residue from a broken tablet.
- If you touch a broken tablet, wash the area thoroughly with soap and water.
- If any [TRADENAME] gets in your eyes, wash your eyes right away with water for at least 15 minutes, and call your healthcare provider right away.
- Call your healthcare provider right away in case of a skin reaction.

What are the possible side effects of [TRADENAME]?

See “What is the most important information I should know about [TRADENAME]?”

[TRADENAME] may cause serious side effects, including:

Low blood cell counts.

[TRADENAME] lessens the number of blood cells that fight infection, help your blood to clot, and carry oxygen throughout your body. This can result in

- Infection
- Bleeding
- Tiredness.

Avoid activities that can raise your chances of these conditions. Your healthcare provider will check your blood counts so that you will know when you are most at risk for infection, bleeding, and tiredness.

Call your healthcare provider right away if you have a temperature of 100.5 F. or above or do not feel well. Do not take a fever medicine until you check with your healthcare provider.

[TRADENAME] may cause other side effects, including:

- nausea and vomiting
- loss of appetite
- skin rash
- swelling in your legs
- diarrhea
- redness and irritation inside your mouth (stomatitis)
- abdominal and muscle pain.

Tell your healthcare provider if you have any side effect that bothers you or that does not go away. These are not all the possible side effects of [TRADENAME]. For more information, ask your healthcare provider or pharmacist.

Call your doctor for medical advice about side effects. You may report side effects to the FDA at 1-800-FDA-1088.

How should I store and throw away [TRADENAME]?

- Store [TRADENAME] at 59-86°F (15-30°C).
- Keep under normal light in a child-resistant container.
- Safely throw away medicine that is out of date or no longer needed.
- Do not put [TRADENAME] in your regular household trash.
- Ask your healthcare provider or pharmacist for directions about how to safely throw away and handle [TRADENAME].

Keep [TRADENAME] and all medicines out of the reach of children.

General information about [TRADENAME]

Medicines are sometimes prescribed for conditions that are not mentioned in patient information. Do not use [TRADENAME] for a condition for which it was not prescribed. Do not give [TRADENAME] to other people, even if they have the same symptoms you have. It may harm them.

This patient information leaflet summarizes the most important information about [TRADENAME]. For more information about [TRADENAME], talk with your healthcare provider. You can ask your healthcare provider or pharmacist for information about [TRADENAME] that is written for health professionals. For more information go to www.fludarabine.com or call 1-8XX-XXX-XXXX.

What are the ingredients in [TRADENAME]?

Active ingredients: fludarabine phosphate

Inactive ingredients: microcrystalline cellulose, lactose monohydrate, colloidal anhydrous silicon dioxide, croscarmellose sodium and magnesium stearate. The film-coat contains hypromellose, talc, titanium dioxide (E171) and ferric oxide pigment (red/E172, yellow/E172).

Rx only

PPI Issued August 11, 2008

Antisoma Research Ltd